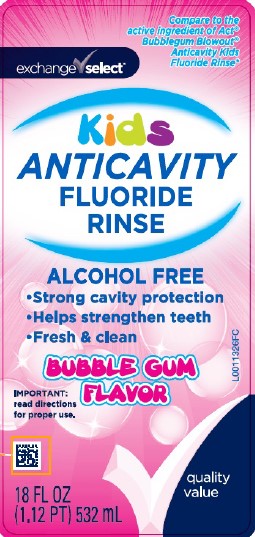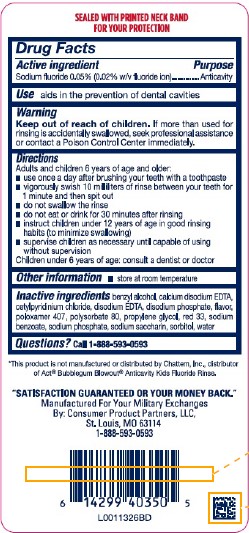 DRUG LABEL: Kids  Flouride Rinse
NDC: 55301-004 | Form: RINSE
Manufacturer: Your Military Exchanges
Category: otc | Type: HUMAN OTC DRUG LABEL
Date: 20260212

ACTIVE INGREDIENTS: SODIUM FLUORIDE 0.2 mg/1 mL
INACTIVE INGREDIENTS: BENZYL ALCOHOL; EDETATE CALCIUM DISODIUM; CETYLPYRIDINIUM CHLORIDE; EDETATE DISODIUM ANHYDROUS; SODIUM PHOSPHATE, DIBASIC, ANHYDROUS; POLOXAMER 407; POLYSORBATE 80; PROPYLENE GLYCOL; D&C RED NO. 33; SODIUM BENZOATE; SODIUM PHOSPHATE; SACCHARIN SODIUM; SORBITOL; WATER

Exchange Select 004.002/004AE
Anticavity Fluoride Rinse, Bubble Gum

Tamper Evident Statement

SEALED WITH PRINTED NECK BAND FOR YOUR PROTECTION

Active ingredient

Sodium Fluoride 0.05% (0.02% w/v fluoride ion)

Purpose

Anticavity

Use

aids in the prevention of dental cavities

Warnings

for this product

Keep out of reach of children.

If more than used for rinsing is accidentally swallowed, seek professional assistance or contact a Poison Control Center immediately.

Directions

Adults and children 6 years of age and older:

- use once a day after brushing your teeth with a toothpaste
- vigorously swish 10 milliliters of rinse between your teeth for 1 minute and then spit out
- do not swallow the rinse
- do not eat or drink for 30 minutes after rinsing
- instruct children under 12 years of age in good rinsing habits (to minimize swallowing)
- supervise children as necessary until capable of using without supervision

Children under 6 years of age: consult a dentist or doctor

Other information

- store at room temperature

Inactive ingredients

benzyl alcohol, calcium disodium EDTA, cetylpyridinium chloride, disodium EDTA, disodium phosphate, flavor, poloxamer 407, polysorbate 80, propylene glycol, red 33, sodium benzoate, sodium phosphate, sodium saccharin, sorbitol, water

Questions?

Call 1-888-593-0593

Disclaimer

*This is not manufactured or distributed by Chattem, Inc., distributor of Act® Bubblegum Blowout®Anticavity Kids Fluoride Rinse.

Adverse reactions

"SATISFACTION GUARANTEED OR YOUR MONEY BACK."

Manufactured For Your Military Exchanges

By: Consumer Product Partners, LLC,

St. Louis, MO 83114

1-888-593-0593

principal display panel

Compare to the active ingredient of Act®Bubblegum Blowout®Anticavity Kids Fluoride Rinse*

exchange select™

KIDS ANTICAVITY FLUORIDE RINSE

ALCOHOL FREE

- Strong cavity protection
- Helps strengthen teeth
- Fresh & clean

BUBBLE GUM FLAVOR

IMPORTANT: read directions for proper use.

quality value

18 FL OZ (1.12 PT) 532 mL